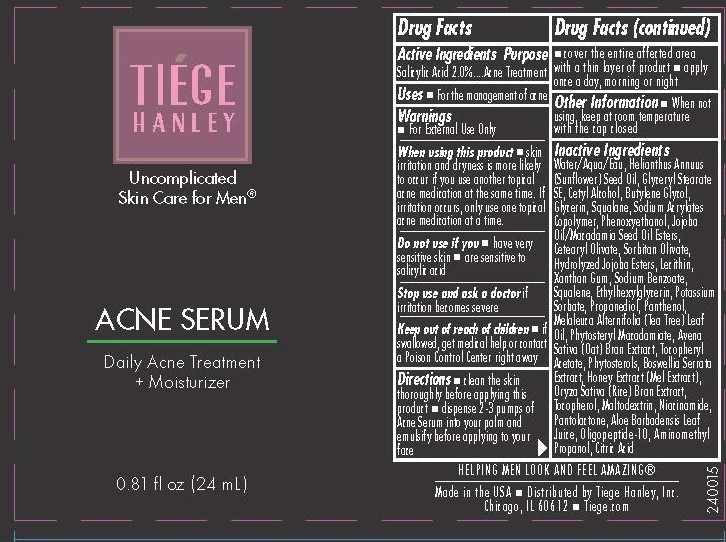 DRUG LABEL: Tiege Hanley
NDC: 71714-003 | Form: CREAM
Manufacturer: Tiege Hanley
Category: otc | Type: HUMAN OTC DRUG LABEL
Date: 20251015

ACTIVE INGREDIENTS: SALICYLIC ACID 20 mg/1 mL
INACTIVE INGREDIENTS: GLYCERYL STEARATE SE; GLYCERIN; HYDROLYZED JOJOBA ESTERS (ACID FORM); ETHYLHEXYLGLYCERIN; BUTYLENE GLYCOL; PROPANEDIOL; JOJOBA OIL; MELALEUCA ALTERNIFOLIA (TEA TREE) LEAF OIL; SODIUM ACRYLATES CROSSPOLYMER-2; SORBITAN OLIVATE; ORYZA SATIVA WHOLE; .ALPHA.-TOCOPHEROL, D-; PANTOLACTONE; PHENOXYETHANOL; AVENA SATIVA FLOWERING TOP; PANTHENOL; MALTODEXTRIN; ANHYDROUS CITRIC ACID; AMINOMETHYL PROPANEDIOL; CETYL ALCOHOL; XANTHAN GUM; NIACINAMIDE; ALOE VERA LEAF; SQUALANE; CETEARYL OLIVATE; PHYTOSTERYL MACADAMIATE; OLIGOPEPTIDE-10; POTASSIUM SORBATE; .ALPHA.-TOCOPHERYLOXYACETIC ACID; BOSWELLIA SERRATA RESIN OIL; HONEY; SUNFLOWER SEED OIL GLYCERETH-8 ESTERS; LECITHIN, SOYBEAN; SODIUM BENZOATE; SQUALENE; WATER

Tiege Hanley Acne Serum

ACTIVE INGREDIENT

Salicylic Acid 2%

Keep out of reach of children. If swallowed, get medical help or contact a Poison Control Center right away.

PURPOSE

Acne Treatment

Directions
■ clean the skin
thoroughly before applying this
product
■ dispense 2-3 pumps of
Acne Serum into your palm and
emulsify before applying to your face
■cover the entire affected area
with a thin layer of product
■ apply once a day, morning or night

INDICATIONS AND USAGE

Uses ■ For the management of acne

Warnings
■ For External Use Only
When using this product ■ skin
irritation and dryness is more likely
to occur if you use another topical
acne medication at the same time. If
irritation occurs, only use one topical
acne medication at a time.
Do not use if you ■ have very
sensitive skin ■ are sensitive to
salicylic acid
Stop use and ask a doctor if
irritation becomes severe
Keep out of reach of children ■ if
swallowed, get medical help or contact
a Poison Control Center right away

Inactive Ingredients:
Water/Aqua/Eau, Helianthus Annuus
(Sunflower) Seed Oil, Glyceryl Stearate
SE, Cetyl Alcohol, Butylene Glycol,
Glycerin, Squalane, Sodium Acrylates
Copolymer, Phenoxyethanol, Jojoba
Oil/Macadamia Seed Oil Esters,
Cetearyl Olivate, Sorbitan Olivate,
Hydrolyzed Jojoba Esters, Lecithin,
Xanthan Gum, Sodium Benzoate,
Squalene, Ethylhexylglycerin, Potassium
Sorbate, Propanediol, Panthenol,
Melaleuca Alternifolia (Tea Tree) Leaf
Oil, Phytosteryl Macadamiate, Avena
Sativa (Oat) Bran Extract, Tocopheryl
Acetate, Phytosterols, Boswellia Serrata
Extract, Honey Extract (Mel Extract),
Oryza Sativa (Rice) Bran Extract,
Tocopherol, Maltodextrin, Niacinamide,
Pantolactone, Aloe Barbadensis Leaf
Juice, Oligopeptide-10, Aminomethyl
Propanol, Citric Acid